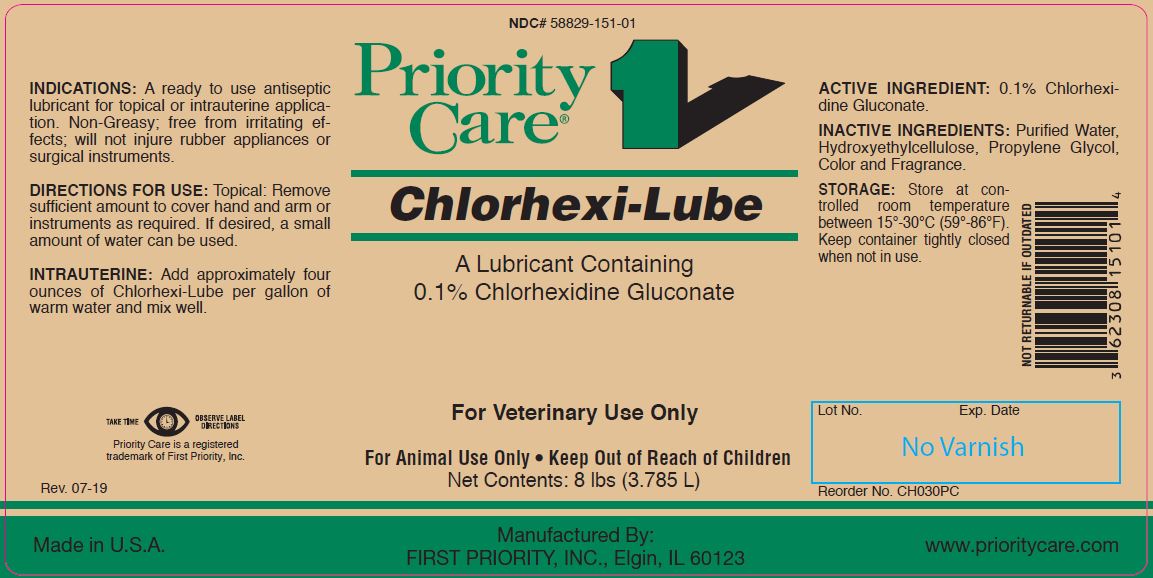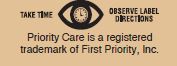 DRUG LABEL: CHLORHEIX-LUBE
NDC: 58829-151 | Form: JELLY
Manufacturer: FIRST PRIORITY INCORPORATED
Category: animal | Type: OTC ANIMAL DRUG LABEL
Date: 20260218

ACTIVE INGREDIENTS: CHLORHEXIDINE GLUCONATE 5.26 g/1 L

Chlorhexi-Lube

PURPOSE

A Lubricant Containing 0.1% Chlorhexidine Gluconate

KEEP OUT OF REACH OF CHILDREN

For Veterinary Use Only

For Animal Use Only • Keep Out of Reach of Children

INDICATIONS:

A ready to use antiseptic lubricant for topical or intrauterine application. Non-Greasy; free from irritating effects; will not injure rubber appliances or surgical instruments.

DIRECTIONS FOR USE:

Topical: Remove sufficient amount to cover hand and arm or instruments as required. If desired, a small amount of water can be used.

INTRAUTERINE:

Add approximately four ounces of Chlorhexi-Lube per gallon of warm water and mix well.

ACTIVE INGREDIENT:

0.1% Chlorhexidine Gluconate.

STORAGE:

Store at controlled room temperature between 15°-30°C (59°-86°F). Keep container tightly closed when not in use.

Net Contents:

8 lbs (3.785 L) Reorder No. CH030PC

INFORMATION FOR OWNERS/CAREGIVERS

Priority Care is a registered trademark of First Priority, Inc.

Manufactured By: FIRST PRIORITY, INC., Elgin, IL 60123-1146